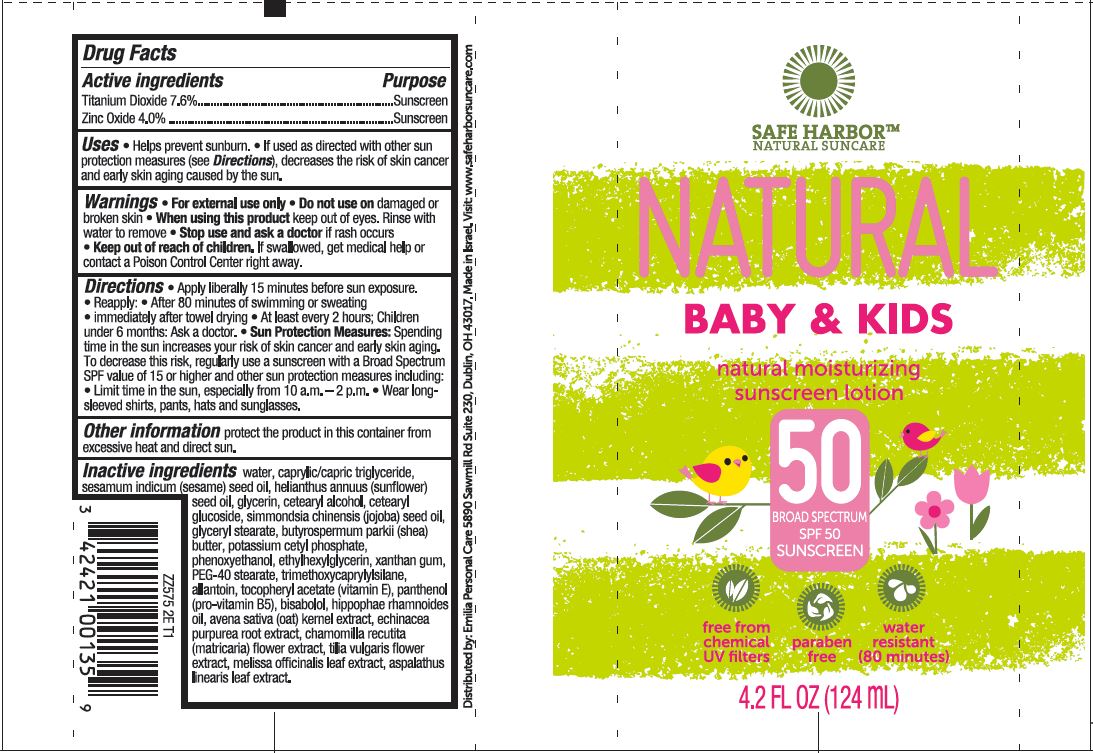 DRUG LABEL: Safe Harbor Natural Suncare
NDC: 42421-575 | Form: LOTION
Manufacturer: Emilia Personal Care Inc
Category: otc | Type: HUMAN OTC DRUG LABEL
Date: 20151120

ACTIVE INGREDIENTS: TITANIUM DIOXIDE 9.4 g/124 g; ZINC OXIDE 4.96 g/124 g
INACTIVE INGREDIENTS: WATER; MEDIUM-CHAIN TRIGLYCERIDES; SESAME OIL; GLYCERIN; CETOSTEARYL ALCOHOL; CETEARYL GLUCOSIDE; JOJOBA OIL; GLYCERYL 1-STEARATE; SHEA BUTTER; POTASSIUM CETYL PHOSPHATE; PHENOXYETHANOL; ETHYLHEXYLGLYCERIN; XANTHAN GUM; PEG-40 STEARATE; TRIMETHOXYCAPRYLYLSILANE; ALLANTOIN;  .ALPHA.-TOCOPHEROL ACETATE   ; PANTHENOL; LEVOMENOL; HIPPOPHAE RHAMNOIDES SEED OIL; OAT; ECHINACEA PURPUREA ROOT; MATRICARIA RECUTITA ROOT; TILIA X EUROPAEA FLOWER; MELISSA OFFICINALIS LEAF; ASPALATHUS LINEARIS LEAF

Drug Facts

Active ingredients

Titanium Dioxide 7.6%

Zinc Oxide 4.0%

Purpose

Sunscreen

Sunscreen

INDICATIONS AND USAGE

Uses -Helps prevent sunburn -If used as directed with other sun

protection measures (see Directions) decreases the risk of skin cancer

and early skin aging caused by the sun.

WARNINGS

Warnings -For external use only -Do not use on damaged or

broken skin -When using this product keep out of eyes. Rinse with

water to remove -Stop use and ask a doctor if rash occurs

Keep out of reach of children. If swallowed, get medical help or

contact a Poison Control Center right away.

DOSAGE AND ADMINISTRATION

Directions -Apply liberally 15 minutes before sun exposure.

-Reapply -After 80 minutes of swimming or sweating

-immediately after towel drying -At least every 2 hours; Children

under 6 months: Ask a doctor. -Sun Protection Measures: Spending

time in the sun increases your risk of skin cancer and early skin aging.

To decrease this risk, regularly use a sunscreen with a Broad Spectrum

SPF value of 15 or higher and other sun protection measures including:

-Limit time in the sun, especially from 10 a.m. - 2 p.m. -Wear long-

sleeved shirts, pants, hats and sunglasses.

Other information protect the product in this container from

excessive heat and direct sun

Inactive ingredients water, caprylic/capric triglyceride, sesamum

indicum (sesame) seed oil, helianthus annuus

(sunflower) seed oil, glycerin, cetearyl alcohol,

cetearyl glucoside, simmondsia chinensis

(jojaba) seed oil, glyceryl stearate,

butyrosperum parkii (shea) butter, potassium

cetyl phosphate, phenoxyethanol, ethylhexylglycerin,

xanthan gum, PEG-40 stearate, trimethoxycaprylsilane, allantoin,

tocopherol acetate (vitamin E), panthenol (pro-vitamin B5),

bisabolol, hippophae rhamnoides oil, avena sativa (oat) kernel extract,

echinacea purpurea root extract, chamomilla recutita (matricaria) flower extract,

tilia vulgaris flower extract, melissa officinalis leaf extract,

aspalathus linearis leaf extract